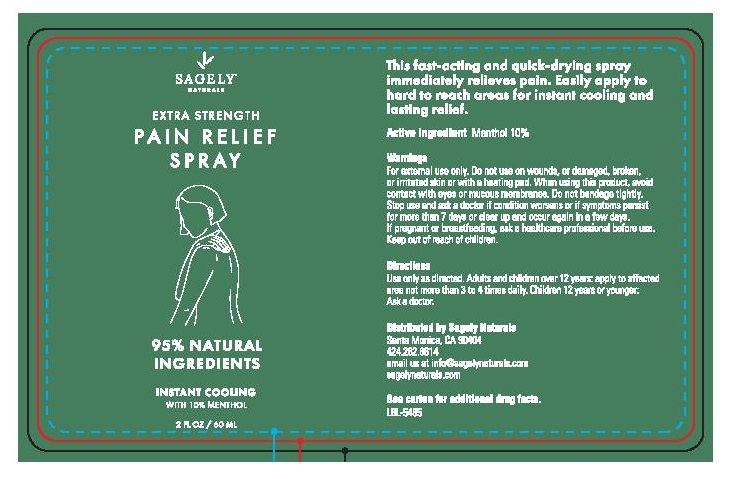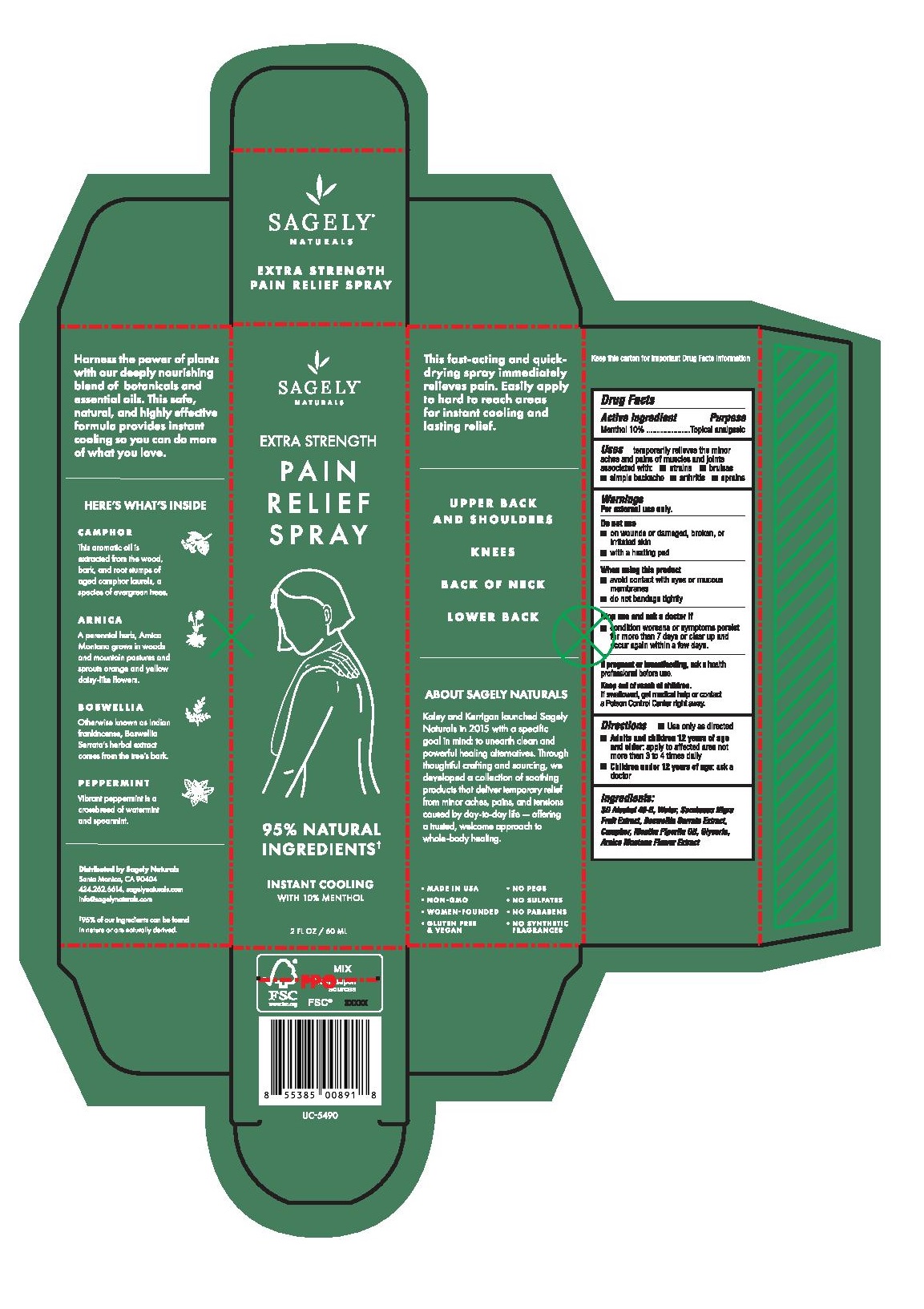 DRUG LABEL: Pain Relief
NDC: 82075-430 | Form: SPRAY
Manufacturer: Sagely Enterprises Inc.
Category: otc | Type: HUMAN OTC DRUG LABEL
Date: 20211203

ACTIVE INGREDIENTS: MENTHOL 10 g/100 g
INACTIVE INGREDIENTS: ARNICA MONTANA FLOWER; ALCOHOL; WATER; INDIAN FRANKINCENSE; EUROPEAN ELDERBERRY; MENTHA PIPERITA; CAMPHOR (NATURAL); GLYCERIN

Pain Relief Spray

Active ingredient

Menthol 10%

Purpose

Menthol 10%...................Topical Analgesic

Uses

temporarily relieves the minor aches and pains of muscles and joints associated with:

- strains
- bruises
- simple backache
- arthritis
- sprains

Warnings

For external use only.

Do not use

- on wounds or damaged, broken, or irritated skin
- with a heating pad

When using this product

- avoid contact with eyes or mucous membranes
- do not bandage tightly

Stop use and ask a doctor if

- condition worsens or symptoms persist for more than 7 days or clear up and occur again within a few days

PREGNANCY OR BREAST FEEDING

If pregnant or breastfeeding, ask a health professional before use.

Keep out of reach of children. If swallowed, get medical help or contact a Poison Control Center right away.

Directions

- Use only as directed
- Adults and children 12 years of age and older: apply to affected area not more than 3 to 4 times daily
- Children under 12 years of age: ask a doctor

Inactive ingredients

SD Alcohol 40-B, Water, Sambucus Nigra Fruit Extract, Boswellia Serrata Extract, Camphor, Mentha Piperita Oil, Glycerin, Arnica Montana Flower Extract

PACKAGE LABEL

Sagely Naturals

Extra Strength

Pain Relief Spray

95% Natural Ingredients

Instant Cooling

with 10% Menthol

2 Fl Oz / 60 mL